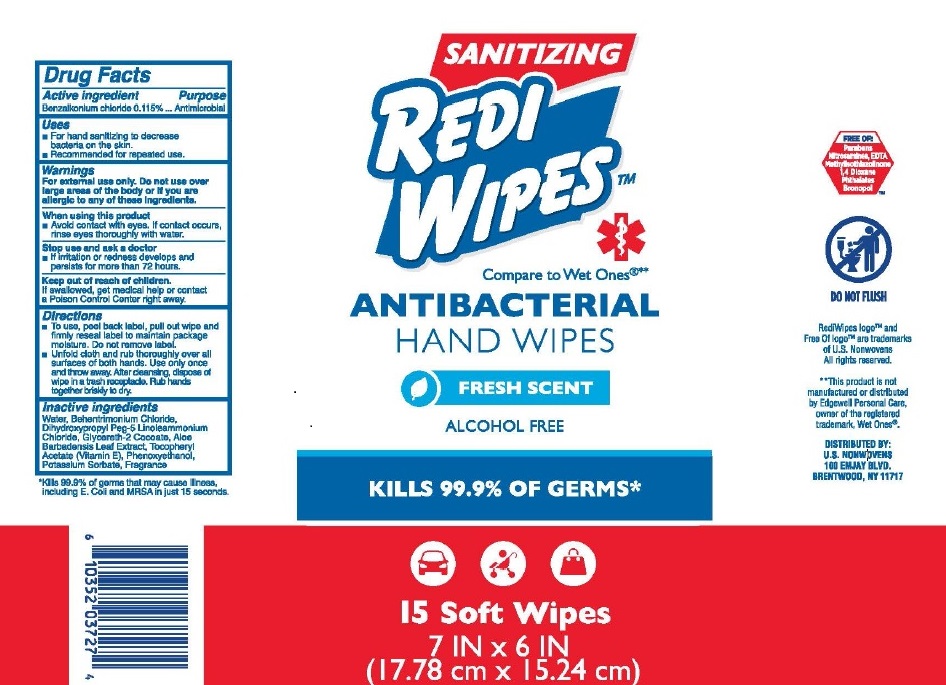 DRUG LABEL: Redi Wipes
NDC: 52553-004 | Form: PATCH
Manufacturer: Radienz Living, LLC
Category: otc | Type: HUMAN OTC DRUG LABEL
Date: 20210419

ACTIVE INGREDIENTS: BENZALKONIUM CHLORIDE 0.115 mg/100 mg
INACTIVE INGREDIENTS: WATER; BEHENTRIMONIUM CHLORIDE; DIHYDROXYPROPYL PEG-5 LINOLEAMMONIUM CHLORIDE; GLYCERETH-2; ALOE VERA LEAF; .ALPHA.-TOCOPHEROL ACETATE; PHENOXYETHANOL; POTASSIUM SORBATE

Redi Wipes Antibacterial Hand Wipes

Active ingredients

Benalkonium chloride (0.115%)

Purpose

Antimicrobial

Uses

- For hand sanitizing to decrease bacteria on the skin.
- Recommended for repeated use.

Warnings

For external use only.

Do not use over large areas of the body or if you are allergic to any of these ingredients.

When using this product

Avoid contact with eyes. If contact occurs, rinse eyes thoroughly with water.

Stop use and ask a doctor if

If irritation or redness develops and persists for more than 72 hours.

Keep out of reach of children.

If swallowed, get medical help or contact a Poison Control Center right away

Directions:

- To use, peel back label, pull out wipe and firmly reseal label to maintain package moisture. Do not remove label.

- Unfold cloth and rub thoroughly over all surfaces of both hands. Use only once and throw away. After cleansing, dispose of wipe in a trash receptacle. Rub hands together briskly to dry.

Inactive ingredients

Water, Behentrimonium Chloride, Dihydroxypropyl Peg-5 Linoleammonium Chloride, Glycereth-2 Cocoate, Aloe Barbadensis Leaf Extract, Tocopheryl Acetate (Vitamin E), Phenoxyethanol, Potassium Sorbate, Fragrance

Other Information

*Kills 99.9% of germs that may cause illness, including E. Coli and MRSA in just 15 seconds.

RediWipes logo™, Free Of logo™, and Wind Energy/Artesian Glacial Aquifer Water logo™ are trademarks of U.S. Nonwovens Corp.
All rights reserved.

**This product is not manufactured or distributed by Edgewell Personal Care, owner of the registered trademark, Wet Ones®.

DISTRIBUTED BY: U.S. NONWOVENS CORP. 100 EMJAY BLVD., BRENTWOOD, NY 11717

Principal Display Panel

SANITIZING REDI WIPESTM

Compare to Wet Ones®**

ANTIBACTERIAL HAND WIPES

FRESH SCENT

ALCOHOL FREE

KILLS 99.9% OF GERMS*

15 Soft Wipes

7 IN x 6 IN

(17.78 cm x 15.24 cm)